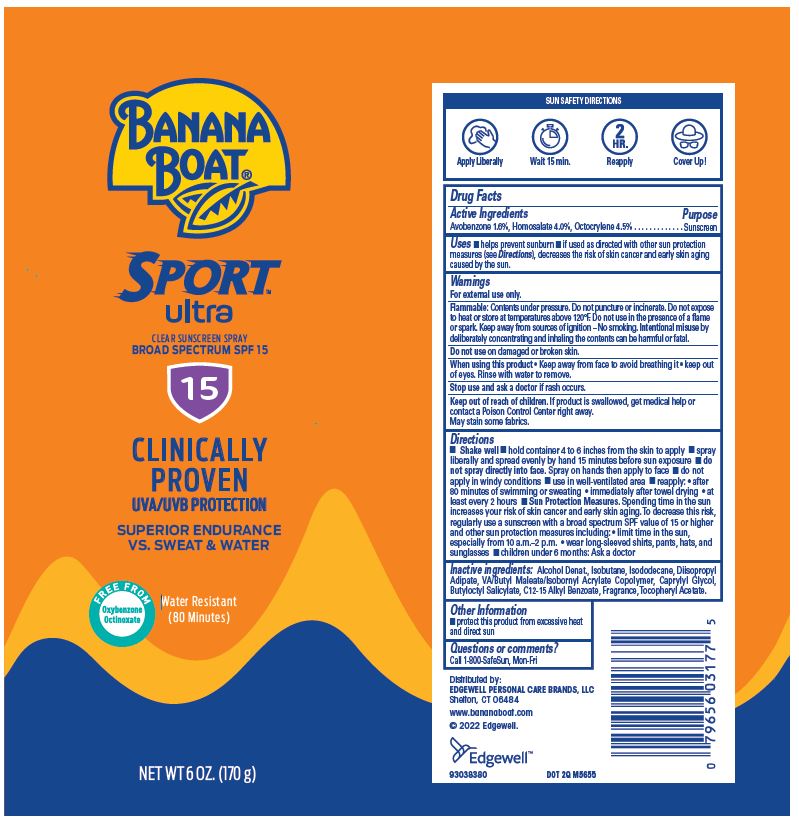 DRUG LABEL: Banana Boat
NDC: 63354-361 | Form: SPRAY
Manufacturer: Edgewell Personal Care Brands LLC
Category: otc | Type: HUMAN OTC DRUG LABEL
Date: 20241027

ACTIVE INGREDIENTS: AVOBENZONE 1.6 g/100 g; HOMOSALATE 4 g/100 g; OCTOCRYLENE 4.5 g/100 g
INACTIVE INGREDIENTS: .ALPHA.-TOCOPHEROL ACETATE; CAPRYLYL GLYCOL; DIISOPROPYL ADIPATE; ALCOHOL; ALKYL (C12-15) BENZOATE; BUTYLOCTYL SALICYLATE; ISOBUTANE; ISODODECANE

Active Ingredients

Avoebenzone 1.6%, Homosalate 4.0%, Octocrylene 4.5%

Purpose

Sunscreen

Uses

• Helps prevent sunburn • if used as directed with other sun protection measures (see Directions), decreases the risk of skin cancer and early skin again caused by the sun.

Warnings

For external use only.

Flammable: Contents under pressure. Do not puncture or incinerate. Do not expose to heat or store at temperatures above 120°F. Do not use in the presence of a flame or spark. Keep away from sources of ignition – No smoking. Intentional misuse by deliberately concentrating and inhaling the contents can be harmful or fatal.

May stain some fabrics.

Do not use

on damaged or broken skin.

When using this product

• Keep away from face to avoid breathing it • keep out of eyes. Rinse with water to remove.

Stop use and ask a doctor

if rash occurs.

Keep out of reach of children

If product is swallowed, get medical help or contact a Posion Control Center right away.

Directions

• Shake well • hold container 4 to 6 inches from the skin to apply • spray liberally and spread evenly by hand 15 minutes before sun exposure • do not spray directly into face. Spray on hands then apply to face • do not apply in windy conditions • use in well-ventialated area • repply: • after 80 minutes of swimming or sweating, immediately after towel drying • at least every 2 hours. Sun Protection Measures. Spending time in the sun increases your risk of skin cancer and early skin aging. To decrease this risk, regularly use a sunscreen with a broad spectrum SPF of 15 or higher and other sun protection measures including: • limit time in the sun, especially from 10 a.m.-2 p.m. • wear long-sleeve shirts, pants, hats, and sunglasses • children under 6 months: Ask a doctor.

Inactive ingredients

Alcohol Denat., Isobutane, Isododecane, Diisopropyl Adipate, VA/Butyl Maleate/Isobornyl Acrylate Copolymer, Caprylyl Glycol, Butyloctyl Salicylate, C12-15 Alkyl Benzoate, Fragrance, Tocopheryl Acetate.

Other Information

• protect this product from excessive heat and direct sun

Questions or comments?

Call 1 800 SafeSun, Mon-Fri

PACKAGE LABEL

BANANA
BOAT®
SPORT
ultra
CLEAR SUNSCREEN SPRAY
BROAD SPECTRUM SPF 15
15
CLINICALLY
PROVEN
UVA/UVB PROTECTION
SUPERIOR ENDURANCE
VS. SWEAT & WATER
FREE FROM
Oxybenzone
Octinoxate
Water Resistant
(80 Minutes)
NET WT 6 OZ. (170 g)